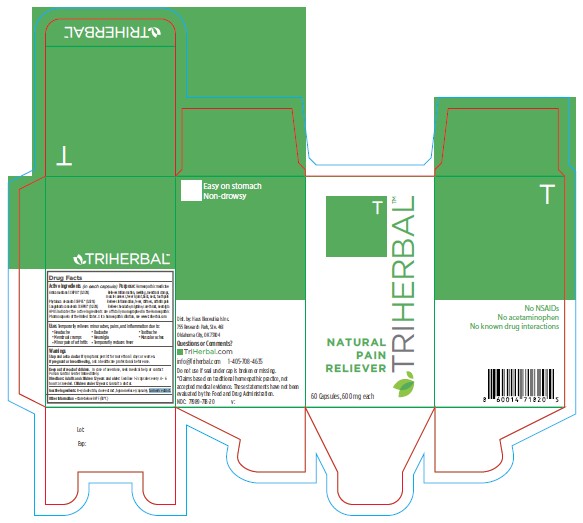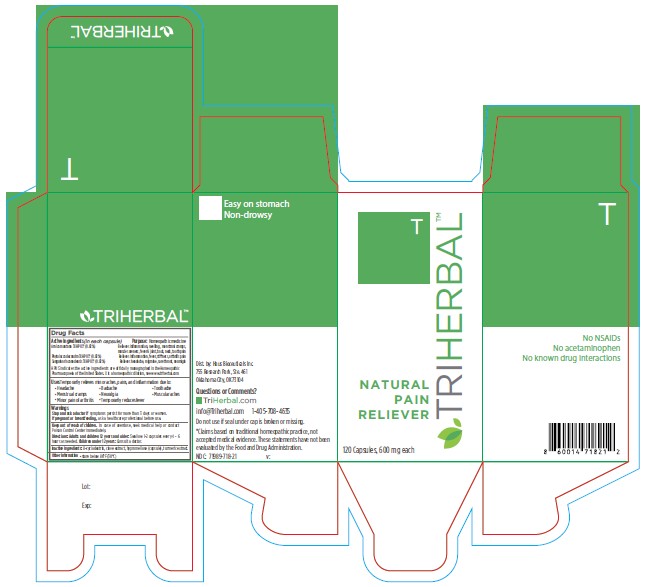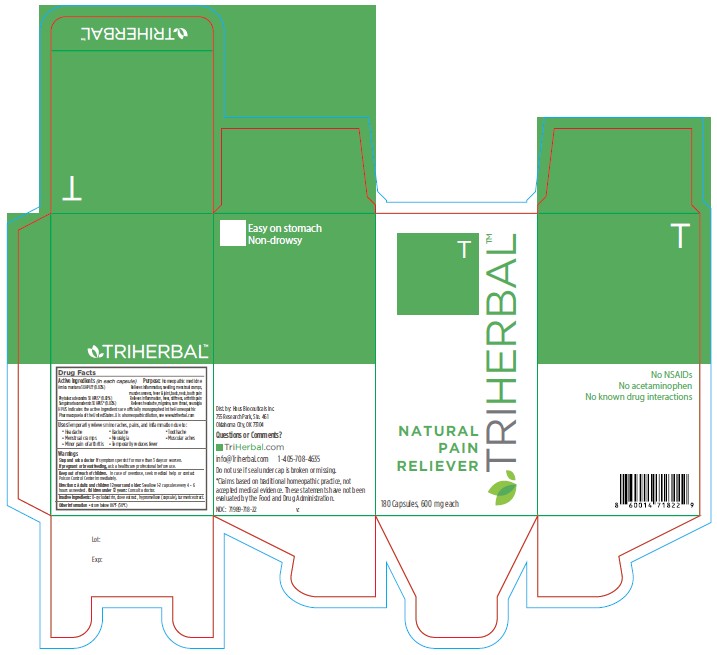 DRUG LABEL: TRIHERBAL
NDC: 71989-718 | Form: CAPSULE
Manufacturer: Spaus Inc.
Category: homeopathic | Type: HUMAN OTC DRUG LABEL
Date: 20251230

ACTIVE INGREDIENTS: ARNICA MONTANA WHOLE 3 [hp_X]/1 1; PHYTOLACCA AMERICANA ROOT 3 [hp_X]/1 1; SANGUINARIA CANADENSIS ROOT 3 [hp_X]/1 1
INACTIVE INGREDIENTS: BETADEX; CLOVE; HYPROMELLOSE, UNSPECIFIED; TURMERIC

TRIHERBAL™ NATURAL PAIN RELIEVER

Active Ingredients (in each capsule)

Arnica montana 3X HPUS* (0.02%)
Phytolacca decandra 3X HPUS* (0.02%)
Sanguinaria canadensis 3X HPUS* (0.02%)
HPUS indicates the active ingredients are officially monographed in the Homeopathic Pharmacopoeia of the United States. X is a homeopathic dilution, see www.triherbal.com

Purpose:

Homeopathic medicine
Relieves Inflammation, swelling, menstrual cramps, muscle soreness, fever & joint, back, neck, tooth pain
Relieves Inflammation, fever, stiffness, arthritis pain
Relieves headache, migraine, sore throat, neuralgia

Uses

Temporarily relieves minor aches, pains, and inflammation due to:

- Headache
- Menstrual cramps
- Minor pain of arthritis
- Backache
- Neuralgia
- Temporarily reduces fever
- Toothache
- Muscular aches

Warnings

Stop and ask a doctor if

symptoms persist for more than 3 days or worsen.

If pregnant or breastfeeding,

ask a healthcare professional before use.

Keep out of reach of children.

In case of overdose, seek medical help or contact Poison Control Center immediately.

Directions:

Adults and children 12 years and older: Swallow 1-2 capsules every 4 – 6 hours as needed.
Children under 12 years: Consult a doctor.

Inactive Ingredients:

ß-cyclodextrin, clove extract, hypromellose (capsule), turmeric extract.

Other Information

- store below 86°F (30°C)

Dist. by: Haus Bioceuticals Inc.
755 Research Park, Ste. 461
Oklahoma City, OK 73104

Questions or Comments? – 60 Count Box Label

TriHerbal.com
info@Triherbal.com 1-405-708-4635
Do not use if seal under cap is broken or missing.
*Claims based on traditional homeopathic practice, not accepted medical evidence. These statements have not been evaluated by the Food and Drug Administration.
NDC: 71989-718-20 v:
No NSAIDs
No acetaminophen
No know drug interactions

Questions or Comments? – 120 Count Box Label

TriHerbal.com
info@Triherbal.com 1-405-708-4635
Do not use if seal under cap is broken or missing.
*Claims based on traditional homeopathic practice, not accepted medical evidence. These statements have not been evaluated by the Food and Drug Administration.
NDC: 71989-718-21 v:
No NSAIDs
No acetaminophen
No know drug interactions

Questions or Comments? – 180 Count Box Label

TriHerbal.com
info@Triherbal.com 1-405-708-4635
Do not use if seal under cap is broken or missing.
*Claims based on traditional homeopathic practice, not accepted medical evidence. These statements have not been evaluated by the Food and Drug Administration.
NDC: 71989-718-22 v:
No NSAIDs
No acetaminophen
No know drug interactions

Package/Label Principal Display Panel – 60 Count Box Label

TRIHERBAL™
NATURAL
PAIN
RELIEVER
60 Capsules, 600 mg each

Package/Label Principal Display Panel – 120 Count Box Label

TRIHERBAL™
NATURAL
PAIN
RELIEVER
120 Capsules, 600 mg each

Package/Label Principal Display Panel – 180 Count Box Label

TRIHERBAL™
NATURAL
PAIN
RELIEVER
180 Capsules, 600 mg each